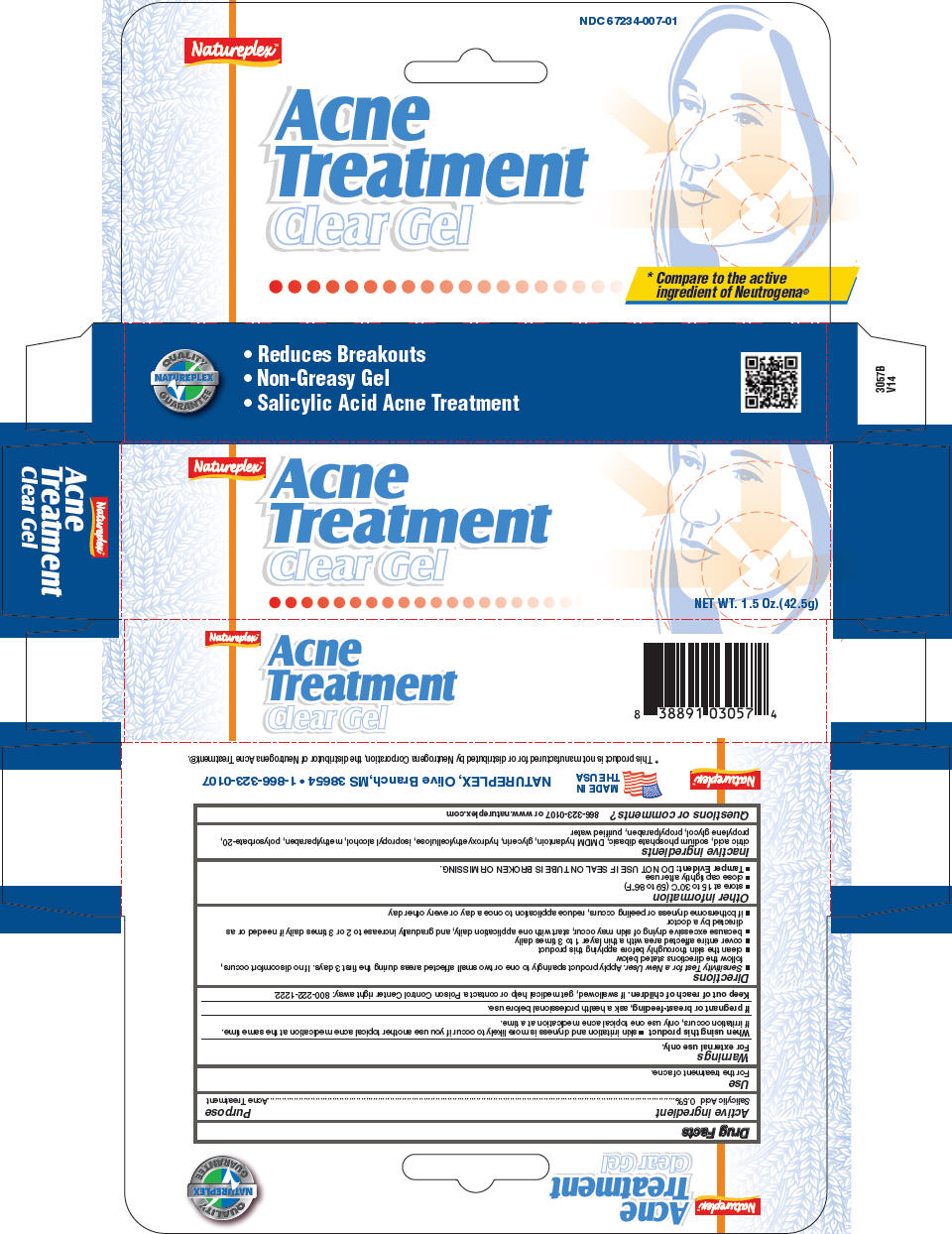 DRUG LABEL: Acne Treatment
NDC: 67234-007 | Form: GEL
Manufacturer: Natureplex, LLC
Category: otc | Type: HUMAN OTC DRUG LABEL
Date: 20260129

ACTIVE INGREDIENTS: SALICYLIC ACID 5 mg/1 g
INACTIVE INGREDIENTS: DMDM HYDANTOIN; GLYCERIN; HYDROXYETHYL CELLULOSE (1500 MPA.S AT 1%); METHYLPARABEN; PROPYLPARABEN; PROPYLENE GLYCOL; WATER

Acne Treatment

Drug Facts

Active ingredient

Salicylic Acid 0.5%

Purpose

Acne Treatment

Use

For the treatment of acne.

Warnings

For external use only.

When using this product

- skin irritation and dryness is more likely to occur if you use another topical acne medication at the same time. If irritation occurs, only use one topical acne medication at a time.

PREGNANCY OR BREAST FEEDING

If pregnant or breast-feeding, ask a health professional before use.

Keep out of reach of children. If swallowed, get medical help or contact a Poison Control Center right away: 800-222-1222.

Directions

- Sensitivity Test for a New User. Apply product sparingly to one or two small affected areas during the first 3 days. If no discomfort occurs, follow the directions stated below
- clean the skin thoroughly before applying this product
- cover entire affected area with a thin layer 1 to 3 times daily
- because excessive drying of skin may occur, start with one application daily, and gradually increase to 2 or 3 times daily if needed or as directed by a doctor
- if bothersome dryness or peeling occurs, reduce application to once a day or every other day

Other information

- store at 15 to 30°C (59 to 86°F)
- close cap tightly after use
- Tamper Evident: DO NOT USE IF SEAL ON TUBE IS BROKEN OR MISSING.

Inactive ingredients

citric acid, sodium phosphate dibasic, DMDM hydantoin, glycerin, hydroxyethylcellulose, isopropyl alcohol, methylparaben, polysorbate-20, propylene glycol, propylparaben, purified water

Questions or comments?

866-323-0107 or www.natureplex.com

PRINCIPAL DISPLAY PANEL - 42.5 g Tube Box

Natureplex™

Acne
Treatment
Clear Gel

NET WT. 1.5 Oz.(42.5g)